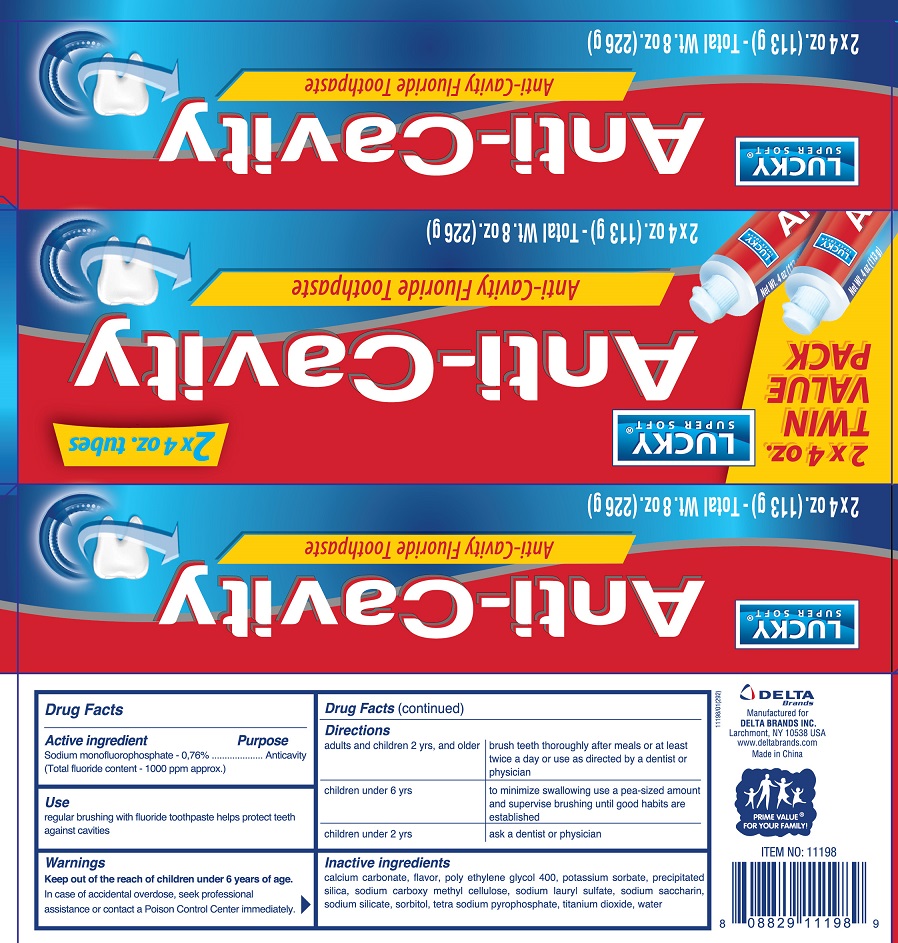 DRUG LABEL: Lucky Super Soft
NDC: 20276-554 | Form: PASTE, DENTIFRICE
Manufacturer: Delta Brands Inc
Category: otc | Type: HUMAN OTC DRUG LABEL
Date: 20181228

ACTIVE INGREDIENTS: SODIUM MONOFLUOROPHOSPHATE 7.6 mg/1 g
INACTIVE INGREDIENTS: CALCIUM CARBONATE; POLYETHYLENE GLYCOL 400; CARBOXYMETHYLCELLULOSE SODIUM; SODIUM LAURYL SULFATE; SACCHARIN SODIUM; SODIUM SILICATE; SORBITOL; SODIUM PYROPHOSPHATE; TITANIUM DIOXIDE; WATER

Drug Facts

Active ingredient

Sodium monofluorophosphate 0.76% (Total fluoride content-1000 ppm approx.)

Purpose

Anticavity

Use

regular brushing with fluoride toothpaste helps protect teeth against cavities

Keep out of the reach of children

under 6 years of age

Warnings

In case of accidental overdose, seek professional assistance or contact a Poison Control Center immediately.

Directions

adults and children 2 yrs and older brush teeth thoroughly after meals or at least twice a day or use as directed by a dentist or physician. children under 6 yrs to minimize swallowing use a pea-sized amount and brushing until good habits are established. children under 2 years: ask a dentist or physician

Inactive ingredients

calcium carbonate, flavor, polyethylene glycol 400, potassium sorbate, precipitated silica, sodium carboxymethyl cellulose, sodium lauryl sulfate, sodium saccharin, sodium silicate, sorbitol, tetra sodium pyrophosphate, titanium dioxide, water